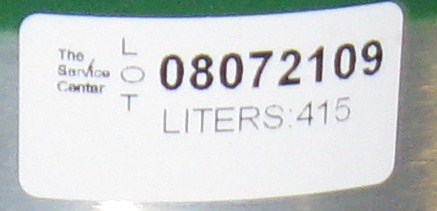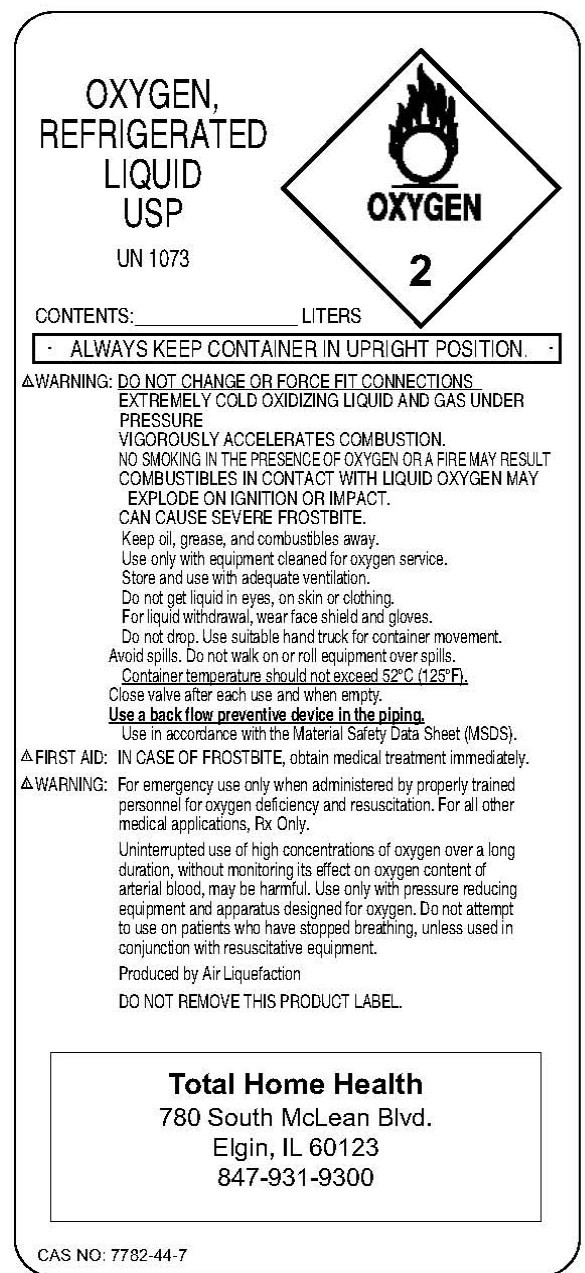 DRUG LABEL: Oxygen
NDC: 62789-0001 | Form: GAS
Manufacturer: THH Acquisition LLC I dba Total Home Health 
Category: prescription | Type: HUMAN PRESCRIPTION DRUG LABEL
Date: 20091118

ACTIVE INGREDIENTS: Oxygen 99 L/100 L

Oxygen